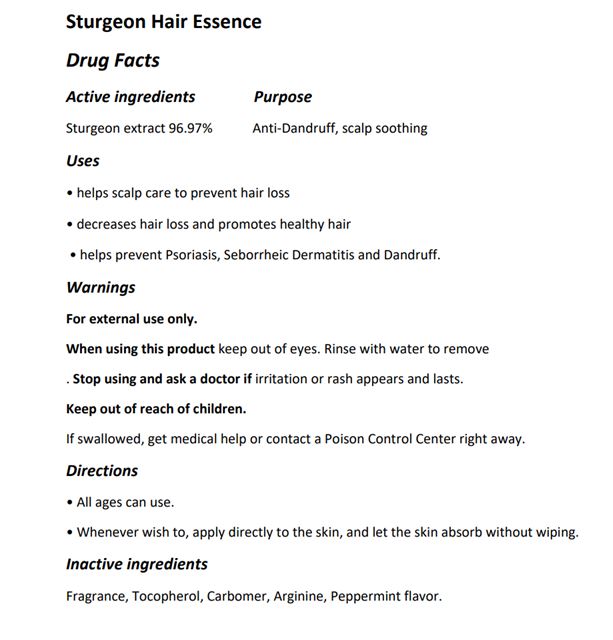 DRUG LABEL: The Zoeun Skin Sturgeon Hair Essence
NDC: 83636-502 | Form: LIQUID
Manufacturer: Sturgeonbio Co.,Ltd.
Category: otc | Type: HUMAN OTC DRUG LABEL
Date: 20240115

ACTIVE INGREDIENTS: STURGEON, UNSPECIFIED 96.97 g/100 mL
INACTIVE INGREDIENTS: TOCOPHEROL; CARBOMER HOMOPOLYMER, UNSPECIFIED TYPE; ARGININE; FRAGRANCE 13576; PEPPERMINT

83636-502 The Zoeun Skin Sturgeon Hair Essence

Active Ingredients

Sturgeon extract 96.97%

Purposes

Anti-Dandruff, scalp soothing

Uses

• helps scalp care to prevent hair loss
• decreases hair loss and promotes healthy hair
• helps prevent Psoriasis, Seborrheic Dermatitis and Dandruff.

Warnings

For external use only

Warnings

Keep out of eyes. Rinse with water to remove.

Warnings

if irritation or rash appears and lasts.

Warnings

If swallowed, get medical help or contact a Poison Control Center right away.

Directions

• All ages can use.

• Whenever wish to, apply directly to the skin, and let the skin absorb without wiping.

Inactive Ingredients

Fragrance, Tocopherol, Carbomer, Arginine, Peppermint flavor.

Display panel

hair essence